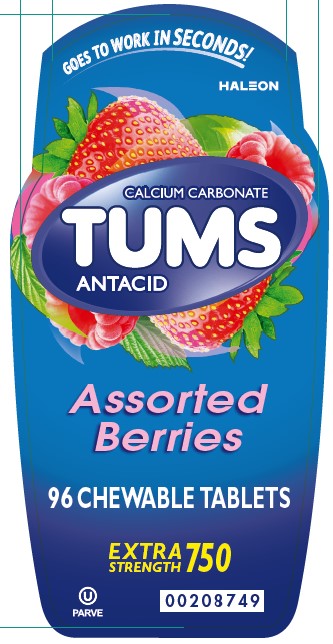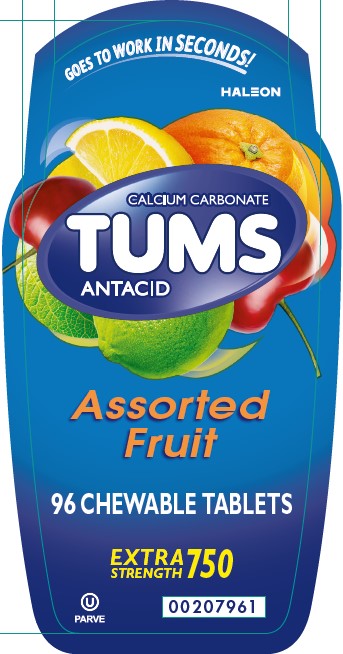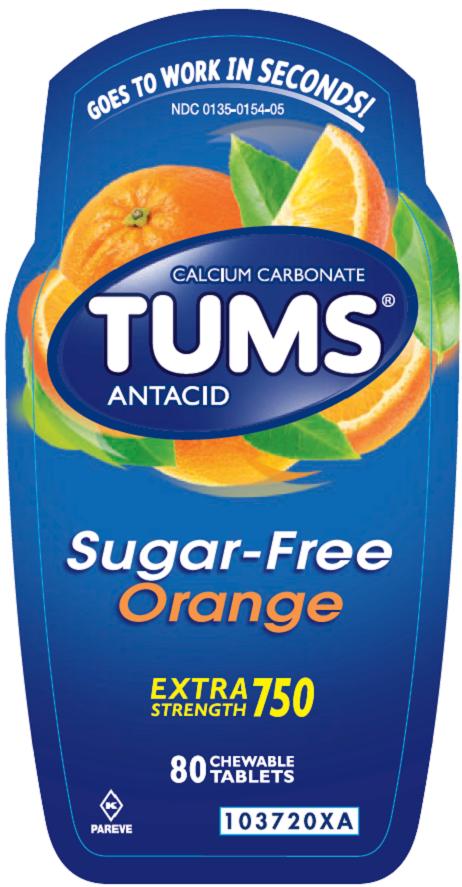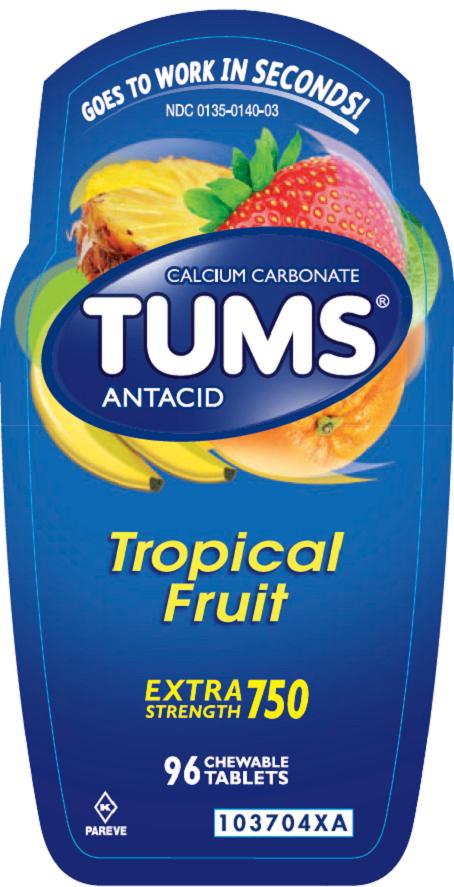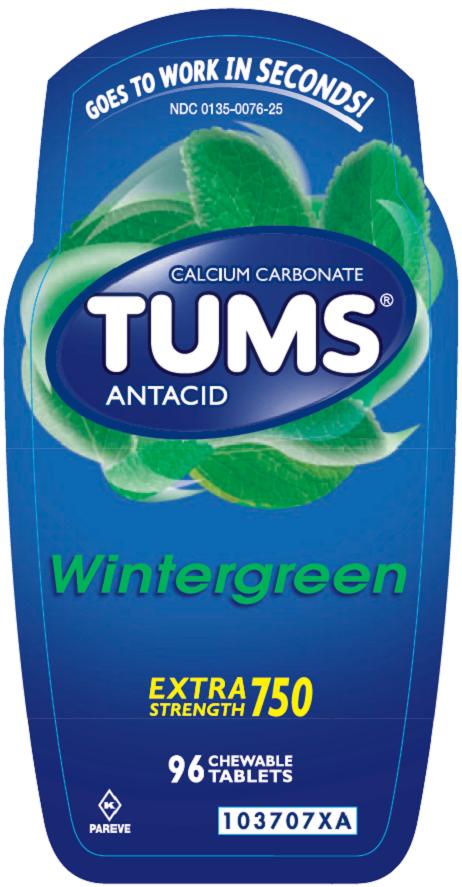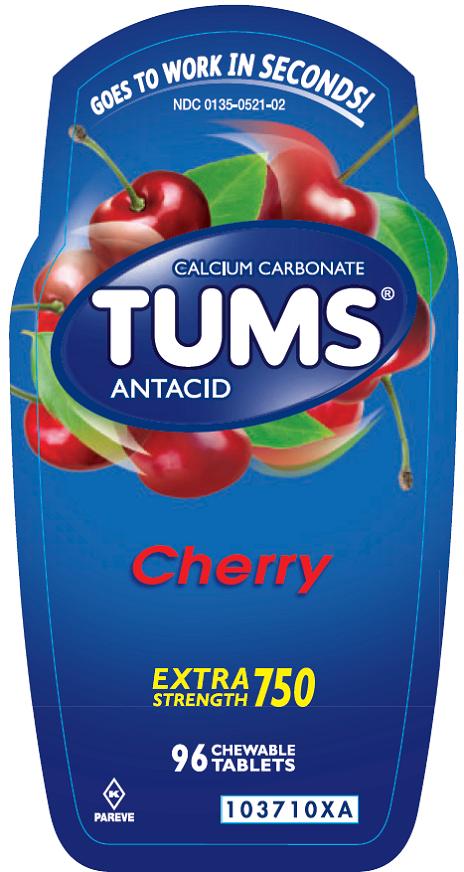 DRUG LABEL: TUMS
NDC: 0135-0074 | Form: TABLET
Manufacturer: Haleon US Holdings LLC
Category: otc | Type: HUMAN OTC DRUG LABEL
Date: 20241205

ACTIVE INGREDIENTS: CALCIUM CARBONATE 750 mg/1 1
INACTIVE INGREDIENTS: ADIPIC ACID; STARCH, CORN; FD&C BLUE NO. 1; ALUMINUM OXIDE; FD&C RED NO. 40; FD&C YELLOW NO. 5; FD&C YELLOW NO. 6; MINERAL OIL; SODIUM POLYMETAPHOSPHATE; SUCROSE; TALC

Drug Facts

Active ingredient (per tablet)

Calcium Carbonate USP 750 mg

Purpose

Antacid

Uses

relieves

- heartburn
- acid indigestion
- sour stomach
- upset stomach associated with these symptoms

Warnings (Assorted Fruit, Assorted Berries, Assorted Tropical Fruit, Wintergreen, Cherry)

Ask a doctor or pharmacist before use if you are

presently taking a prescription drug. Antacids may interact with certain prescription drugs.

When using this product

- do not take more than 10 tablets in 24 hours
- if pregnant do not take more than 6 tablets in 24 hours
- do not use the maximum dosage for more than 2 weeks, except under the advice and supervision of a doctor

Warnings (Sugar Free Orange Cream)

Ask a doctor or pharmacist before use if you are

presently taking a prescription drug. Antacids may interact with certain prescription drugs.

When using this product

- do not take more than 9 tablets in 24 hours
- if pregnant do not take more than 6 tablets in 24 hours
- do not use the maximum dosage for more than 2 weeks, except under the advice and supervision of a doctor

Directions

- adults and children 12 years of age and over: chew 2 – 4 tablets as symptoms occur, or as directed by a doctor. Chew or crush tablets completely before swallowing.
- do not take for symptoms that persist for more than 2 weeks unless advised by a doctor

Other information (Assorted Fruit)

- each tablet contains: elemental calcium 305 mg, magnesium 5 mg, sodium 2mg
- store below 30°C (86°F)
- contains FD&C Yellow No. 5 (tartrazine) as a color additive

Other information (Assorted Berries)

- each tablet contains: elemental calcium 305 mg, magnesium 5 mg, sodium 2mg
- store below 30°C (86°F)

Other information (Assorted Tropical Fruit, Wintergreen, Cherry)

- each tablet contains: elemental calcium 300 mg, sodium 2 mg
- store below 30°C (86°F)

Other information (Orange Cream)

- each tablet contains: elemental calcium 300 mg
- store below 30°C (86°F)

Phenylketonurics: Contains phenylalanine, less than 1mg per tablet.

Inactive ingredients (Assorted Fruit)

adipic acid, corn starch, FD&C blue no. 1 aluminum lake, FD&C red no. 40 aluminum lake, FD&C yellow no. 5 aluminum lake (tartrazine), FD&C yellow no. 6 aluminum lake, flavors, mineral oil, sodium polyphosphate, sucrose, talc

Inactive ingredients (Assorted Berries)

adipic acid, corn starch, FD&C blue #1 lake, FD&C red #40 lake, flavors, mineral oil, sodium polyphosphate, sucrose, talc

Inactive ingredients (Sugar Free Orange Cream)

acacia, adipic acid, aspartame, calcium stearate, FD&C yellow #6 lake, flavors, sorbitol

Inactive ingredient (Assorted Tropical Fruit)

corn starch, FD&C red #40 lake, FD&C yellow #5 (tartrazine) lake, FD&C yellow #6 lake, flavors, mineral oil, sodium polyphosphate, sucrose, talc

Inactive ingredients (Wintergreen)

corn starch, FD&C blue #1 lake, FD&C yellow #5 (tartrazine) lake, flavor, mineral oil, sodium polyphosphate, sucrose, talc

Inactive ingredients (Cherry)

adipic acid, corn starch, FD&C red #40 lake, flavor, mineral oil, sodium polyphosphate, sucrose, talc

Questions?

1-800-897-7535

Do not use if printed inner safety seal under cap is broken or missing.

Gluten-Free

Principal Display Panel (Assorted Fruit)

GOES TO WORK IN SECONDS!

CALCIUM CARBONATE

TUMS

ANTACID

Assorted Fruit

96 CHEWABLETABLETS

EXTRA STRENGTH 750

Principal Display Panel (Assorted Berries)

GOES TO WORK IN SECONDS!

CALCIUM CARBONATE

TUMS

ANTACID

Assorted Berries

96 CHEWABLE TABLETS

EXTRA STRENGTH 750

Principal Display Panel

NDC 0135-0154-05

TUMS®

CALCIUM CARBONATE

ANTACID

Sugar-Free Orange

EXTRA STRENGTH 750

80 CHEWABLE TABLETS

GOES TO WORK IN SECONDS!

PAREVE

©2014 GSK

Front Label: 103720XA

Back Label: 103719XA

Principal Display Panel

NDC 0135-0140-03

TUMS®

CALCIUM CARBONATE

ANTACID

Tropical Fruit

EXTRA STRENGTH 750

96 CHEWABLE TABLETS

GOES TO WORK IN SECONDS!

PAREVE

©2014 GSK

Front Label: 103704XA

Back Label: 103705XA

Principal Display Panel

NDC 0135-0076-25

TUMS®

CALCIUM CARBONATE

ANTACID

Wintergreen

EXTRA STRENGTH 750

96 CHEWABLE TABLETS

GOES TO WORK IN SECONDS!

PAREVE

©2014 GSK

Front Label: 103707XA

Back Label: 103708XA

Principal Display Panel

NDC 0135-0521-02

TUMS®

CALCIUM CARBONATE

ANTACID

Cherry

EXTRA STRENGTH 750

96 CHEWABLE TABLETS

GOES TO WORK IN SECONDS!

PAREVE

©2014 GSK

Front Label: 103710XA

Back Label: 103711XA